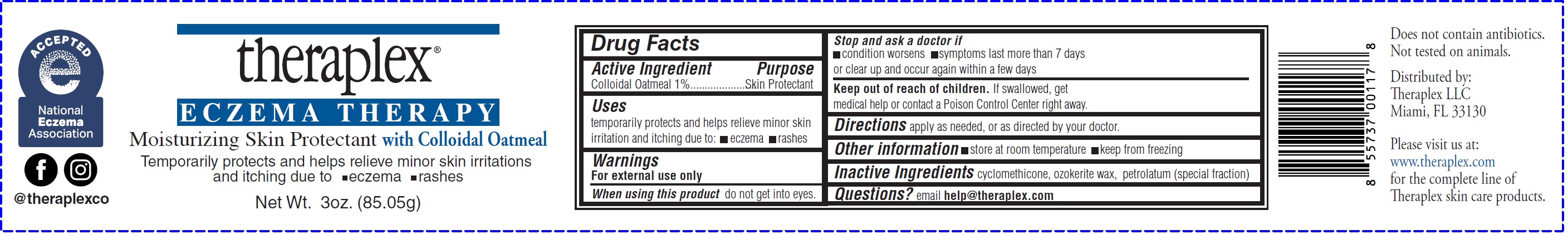 DRUG LABEL: THERAPLEX Eczema Therapy Moisturizing Skin Protectant with Colloidal Oatmeal
NDC: 82280-618 | Form: CREAM
Manufacturer: THERAPLEX, LLC
Category: otc | Type: HUMAN OTC DRUG LABEL
Date: 20250616

ACTIVE INGREDIENTS: OATMEAL 10 mg/1 g
INACTIVE INGREDIENTS: CYCLOMETHICONE; CERESIN; PETROLATUM

THERAPLEX Eczema Therapy Moisturizing Skin Protectant with Colloidal Oatmeal

Active Ingredient

Colloidal Oatmeal 1%

Purpose

Skin Protectant

Uses

temporarily protects and helps relive minor skin irritation and itching due to: • eczema • rashes

Warnings

For external use only

When using this product

do not get into eyes.

Stop use and ask a doctor if

- condition worsens
- symptoms last more than 7 days or clear up and occur again within a few days

Keep out of reach of children.

If swallowed, get medical help or contact a Poison Control Center right away.

Directions

apply as needed, or as directed by your doctor.

Other information

- store at room temperature
- keep from freezing

Inactive Ingredients

cyclomethicone, ozokerite wax, petrolatum (special fraction)

Questions?

email help@theraplex.com